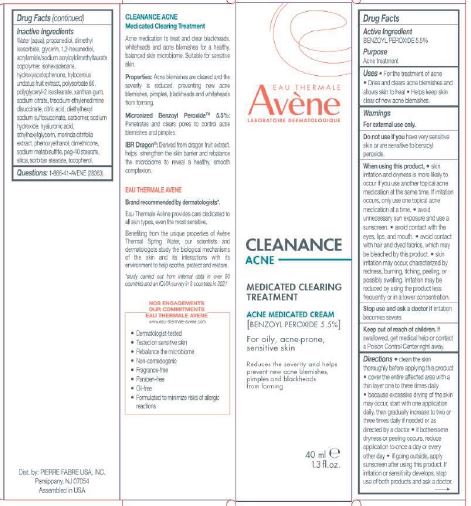 DRUG LABEL: Avene Cleanance Acne Medicated Clearing Treatment
NDC: 64760-776 | Form: LIQUID
Manufacturer: Pierre Fabre USA Inc.
Category: otc | Type: HUMAN OTC DRUG LABEL
Date: 20241106

ACTIVE INGREDIENTS: BENZOYL PEROXIDE 5.5 mg/40 mL
INACTIVE INGREDIENTS: WATER; PROPANEDIOL; DIMETHYL ISOSORBIDE; GLYCERIN; 1,2-HEXANEDIOL; SODIUM ACRYLOYLDIMETHYLTAURATE-ACRYLAMIDE COPOLYMER (1:1; 90000-150000 MPA.S); HYLOCEREUS UNDATUS FRUIT; POLYSORBATE 80; XANTHAN GUM; SODIUM CITRATE; TRISODIUM ETHYLENEDIAMINE DISUCCINATE; CITRIC ACID MONOHYDRATE; SODIUM METABISULFITE; CARBOMER 1342; SODIUM HYDROXIDE; HYALURONIC ACID; PHENOXYETHANOL; DIMETHICONE; PEG-40 STEARATE; HYDRATED SILICA; TOCOPHEROL; HYDROXYACETOPHENONE; MORINDA CITRIFOLIA FRUIT; PEG-20 SORBITAN STEARATE; ISOHEXADECANE; POLYGLYCERYL-2 ISOSTEARATE; DIHEXYL SODIUM SULFOSUCCINATE; ETHYLHEXYLGLYCERIN

Avene Cleanance Acne Medicated Clearing Treatment

Purpose

Acne Treatment

Active Ingredient

BENZOYL PEROXIDE 5.5%

Uses

For the treatment of acne.

Dries and clears acne blemishes and allows skin to heal.

Helps keep skin clear of new acne blemishes

Warnings

For external use only.

Do not use if you

have very sensitive skin or are sensitive to benzoyl peroxide.

When using this product

Skin irritation and dryness is more likely to occur if you use another topical acne medication at the same time. If irritation occurs, only use one topical acne medication at a time.

Avoid unnecessary sun exposure and use a sunscreen.

Avoid contact with the eyes, lips, and mouth.

Avoid contact with hair and dyed fabrics, which may be bleached by this product.

Skin irritation may occur, characterized by redness, burning, itching, peeling, or possibly swelling. Irritation may be reduced by using the product less frequently or in a lower concentration.

Stop use and ask a doctor

If irritation becomes severe

Keep out of reach of children.

If swallowed, get medical help or contact a Poison Control Center right away.

Directions

clean the skin thoroughly before applying this product.

cover the entire affected area with a thin layer one to three times daily.

because excessive dry of the skin may occur, start with one application daily, then gradually increase to two or three times daily needed or as directed by a doctor.

if bothersome dryness or peeling occurs reduce application to once a day or every other day.

if going outside, apply sunscreen after using this product. If irritation or sensitivity develops, stop use of both products and ask a doctor.

Inactive Ingredients

Water (aqua), propanediol, dimethyl isosorbide, glycerin, 1,2-hexanediol, acrylamide/sodium acryloyldimethyllurate copolymer, isohexadecane, hydroxyacetophenone, hylocereus undatus fruit extract, polysorbate 80, polyglyceryl-2 isostearate, xanthan gum, sodium citrate, trisodium ethylenediamine disuccinate, citric acid, diethylhexyl sodium sulfosuccinate, carbomer, sodium hydroxide, hyaluronic acid, ethylhexylglycerin, morinda citrifolia extract, phenoxyethanol, dimethicone, sodium metabisulfite, peg-40 stearate, silica, sorbitan stearate, tocopherol

Questions

1-866-41-AVENE (28363)

Packaging

EAU THERMALE

AVENE

LABORATORIE DERMATOLOGIQUE

CLEANANCE

ACNE

MEDICATED CLEARING

TREATMENT

ACNE MEDICATED CREAM

[BENZOYL PEROXIDE 5.5%

FOR OILY, ACNE-PRONE,

SENSITIVE SKIN

REDUCES THE SEVERITY AND HELPS PREVENT NEW ACNE BLEMISHES, PIMPLES AND BLACKHEADS FROM FORMING

40 ML / 1.3 FL.OZ.